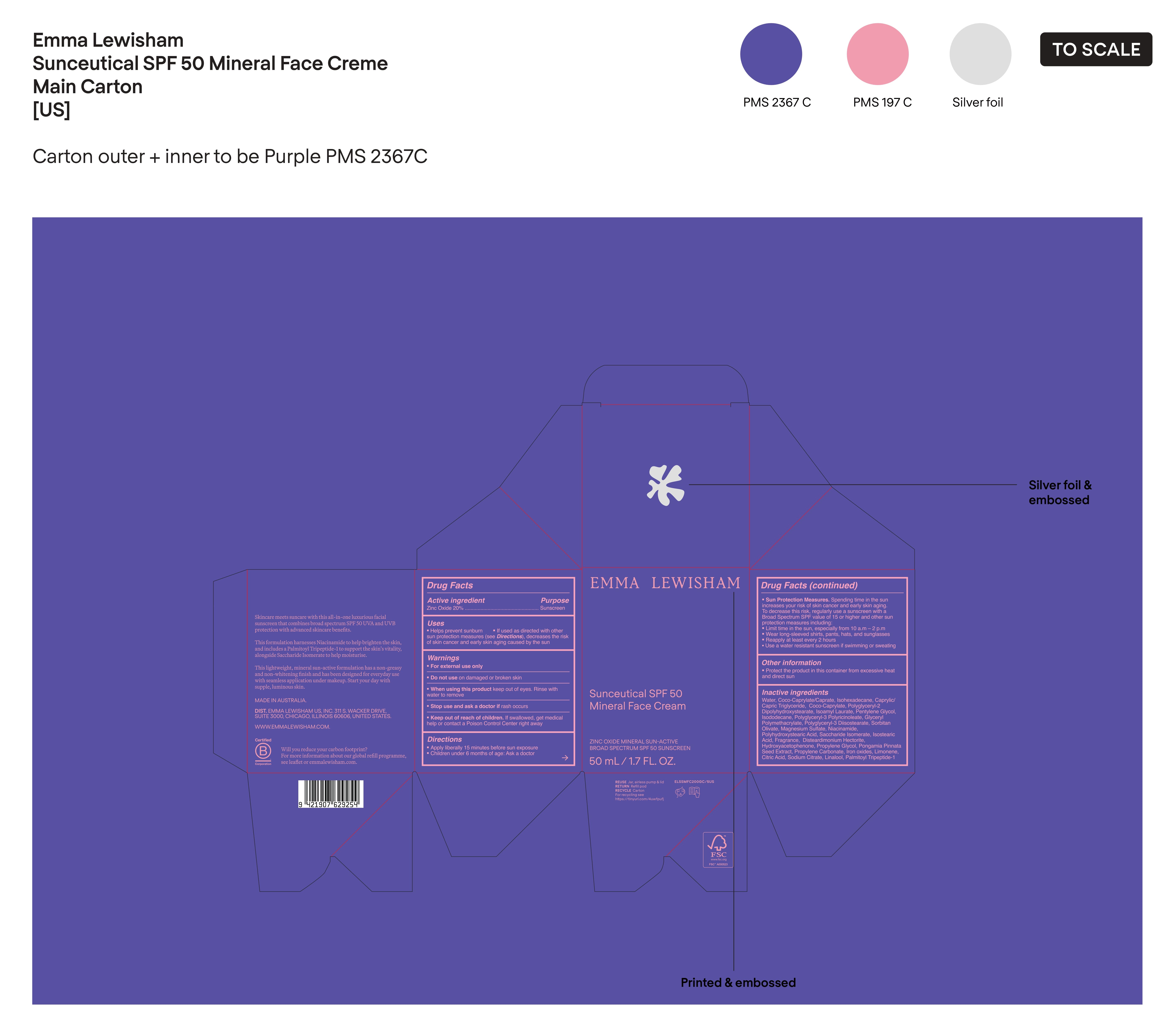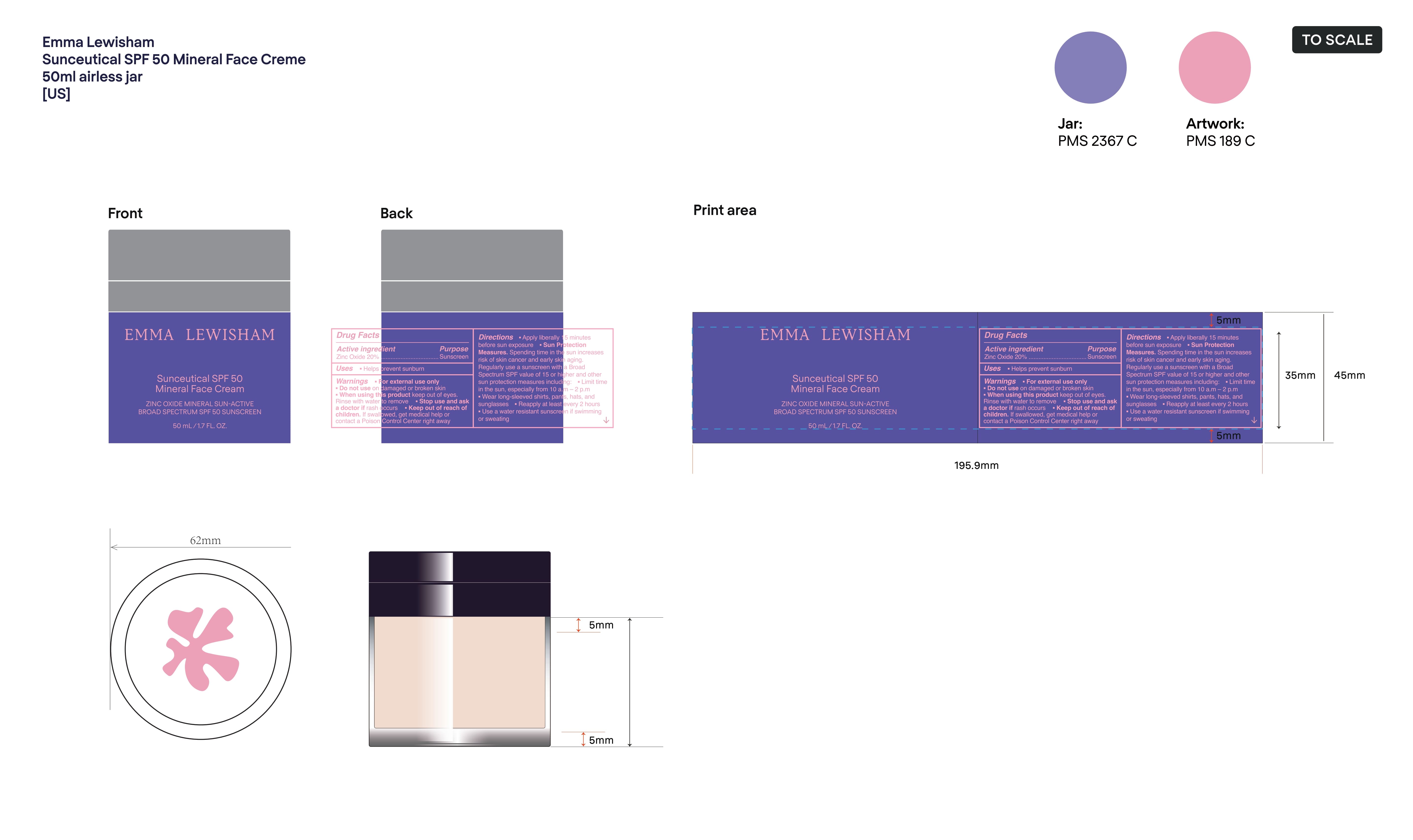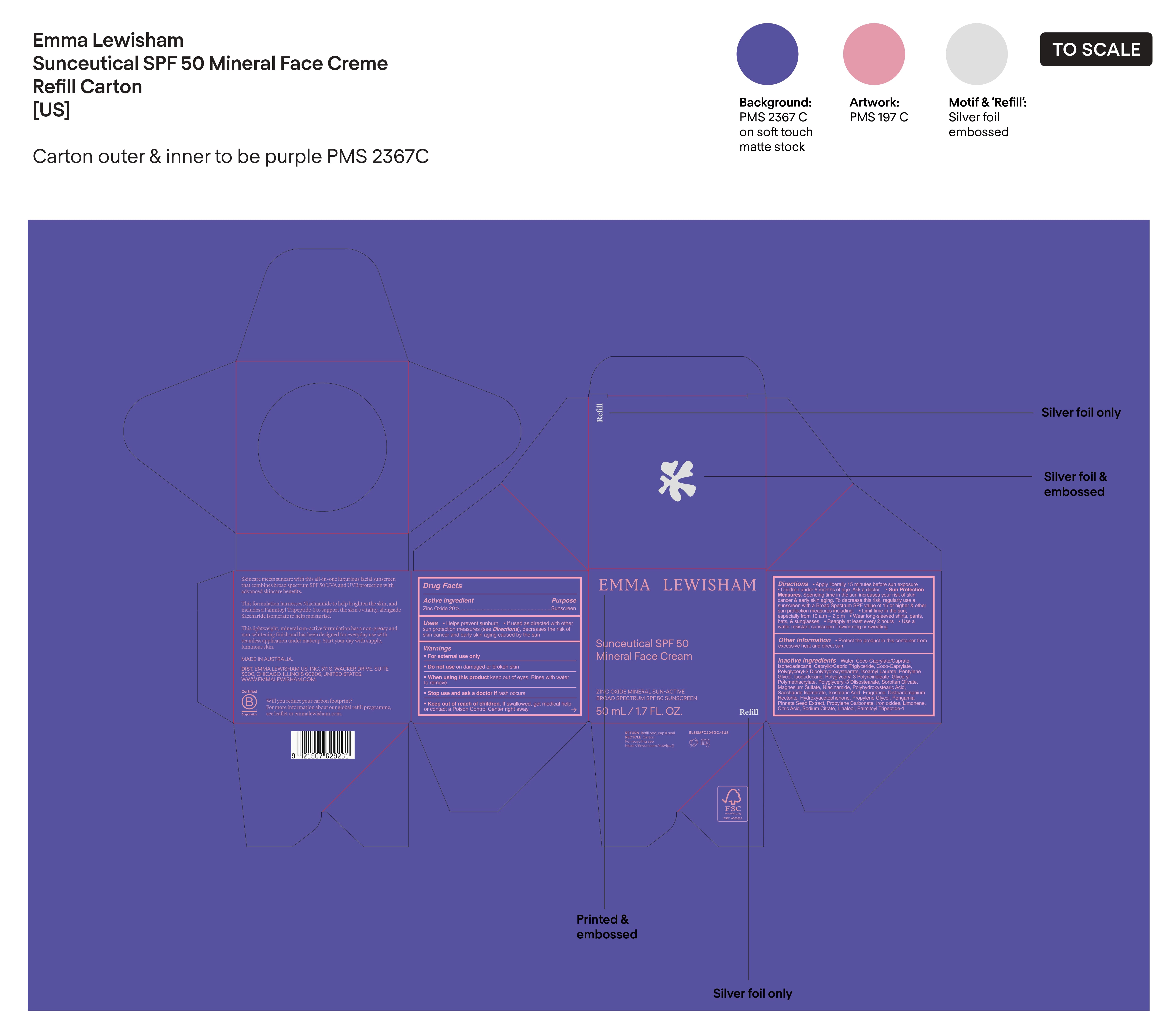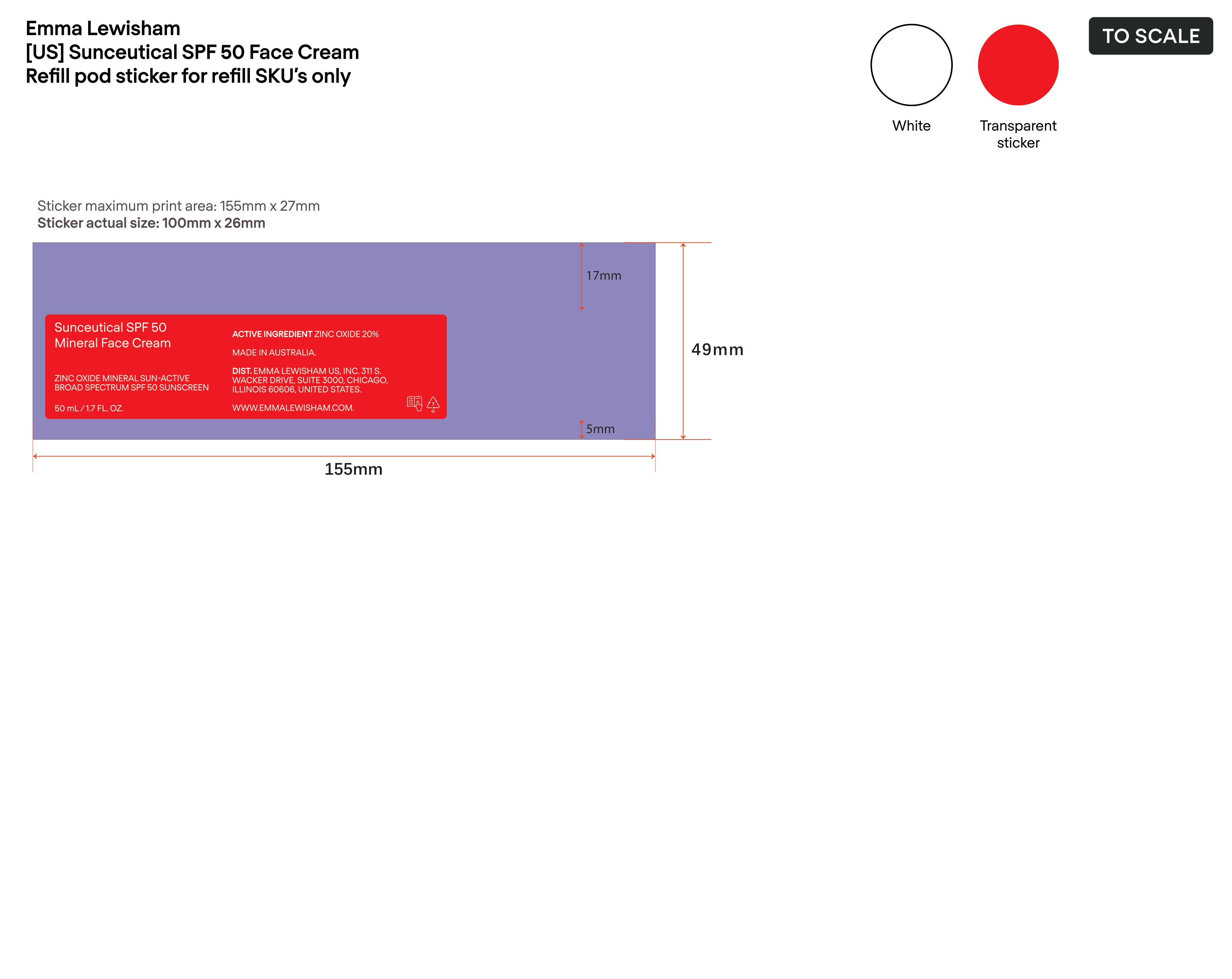 DRUG LABEL: EMMA LEWISHAM Sunceutical SPF 50 Mineral Face Cream
NDC: 84981-005 | Form: LOTION
Manufacturer: EMMA LEWISHAM US, INC.
Category: otc | Type: HUMAN OTC DRUG LABEL
Date: 20250205

ACTIVE INGREDIENTS: ZINC OXIDE 20 g/100 mL
INACTIVE INGREDIENTS: SORBITAN OLIVATE; HYDROXYACETOPHENONE; FERROSOFERRIC OXIDE; POLYGLYCERYL-3 PENTARICINOLEATE; PROPYLENE CARBONATE; PENTYLENE GLYCOL; GLYCERYL POLYMETHACRYLATE (300000 MPA.S); ISOHEXADECANE; LEMON TERPENES; COCO-CAPRYLATE/CAPRATE; MAGNESIUM SULFATE; ISOCYCLEMONE E; PROPYLENE GLYCOL; CAPRYLIC/CAPRIC TRIGLYCERIDE; LINALOOL; FERRIC OXIDE YELLOW; COCO-CAPRYLATE; ISOSTEARIC ACID; WATER; POLYGLYCERYL-2 DIPOLYHYDROXYSTEARATE; LIMONENE, (+)-; ISOAMYL LAURATE; ISODODECANE; NIACINAMIDE; POLYHYDROXYSTEARIC ACID (2300 MW); SACCHARIDE ISOMERATE; SODIUM CITRATE; PONGAMIA PINNATA SEED; LINALYL ACETATE; DISTEARDIMONIUM HECTORITE; FERRIC OXIDE RED; CITRIC ACID; PALMITOYL TRIPEPTIDE-1; POLYGLYCERYL-3 DIISOSTEARATE; HEXAMETHYLINDANOPYRAN

Drug Facts

Active Ingredient

Zinc Oxide 20%

Purpose

Sunscreen

Uses

•Helps prevent sunburn

• If used as directed with other sun protection measures (see Directions), decreases the risk of Skin cancer and early skin aging caused by the sun

Warnings

• For external use only

• Do not use on damaged or broken skin

• When using this product keep out of eyes. Rinse with water to remove

• Stop use and ask a doctor if rash occurs.

• Keep out of reach of children. If swallowed, get medical help or contact a Poison Control Center right away

Directions

• Apply liberally 15 minutes before sun exposure

• Children under 6 months of age: Ask a doctor

• Sun Protection Measures. Spending time in the sun increases your risk of skin cancer and early skin aging. To decrease this risk, regularly use a sunscreen with a Broad spectrum SPF value of 15 or higher and other sun protection measures including:

• Limit time in the sun, especially from 10 a.m. -2 p.m.

• Wear long-sleeved shirts, pants, hats, and sunglasses

• Reapply at least every 2 hours

•Use a water resistant sunscreen if swimming or sweating

Other information

• Protect the product in this container from excessive heat and direct sun

Inactive Ingredients

Water, Coco-Caprylate/Caprate, Isohexadecane, Caprylic/Capric Triglyceride, Coco-Caprylate, Polyglyceryl-2 Dipolyhydroxystearate, Isoamyl Laurate, Pentylene Glycol, Isododecane, Polyglyceryl-3 Polyricinoleate, Glyceryl Polymethacrylate, Polyglyceryl-3 Diisostearate, Sorbitan Olivate, Magnesium Sulfate, Niacinamide, Polyhydroxystearic Acid, Saccharide Isomerate, Isostearic Acid, Fragrance, Disteardimonium Hectorite, Hydroxyacetophenone, Propylene Glycol, Pongamia Pinnata Seed Extract, Propylene Carbonate, Iron Oxides, Limonene, Citric Acid, Sodium Citrate, Linalool, Palmitoyl Tripeptide-1

PRINCIPAL DISPLAY PANEL

EMMA LEWISHAM

Sunceutical SPF 50 Mineral Face Cream

ZINC OXIDE MINERAL SUN-ACTIVE

BROAD SPECTRUM SPF 50 SUNSCREEN

50 mL/1.7 FL. OZ.

PACKAGE LABEL

Sunceutical SPF 50 Mineral Face Cream

ZINC OXIDE MINERAL SUN-ACTIVE

BROAD SPECTRUM SPF 50 SUNSCREEN

50 mL/1.7 FL. OZ.